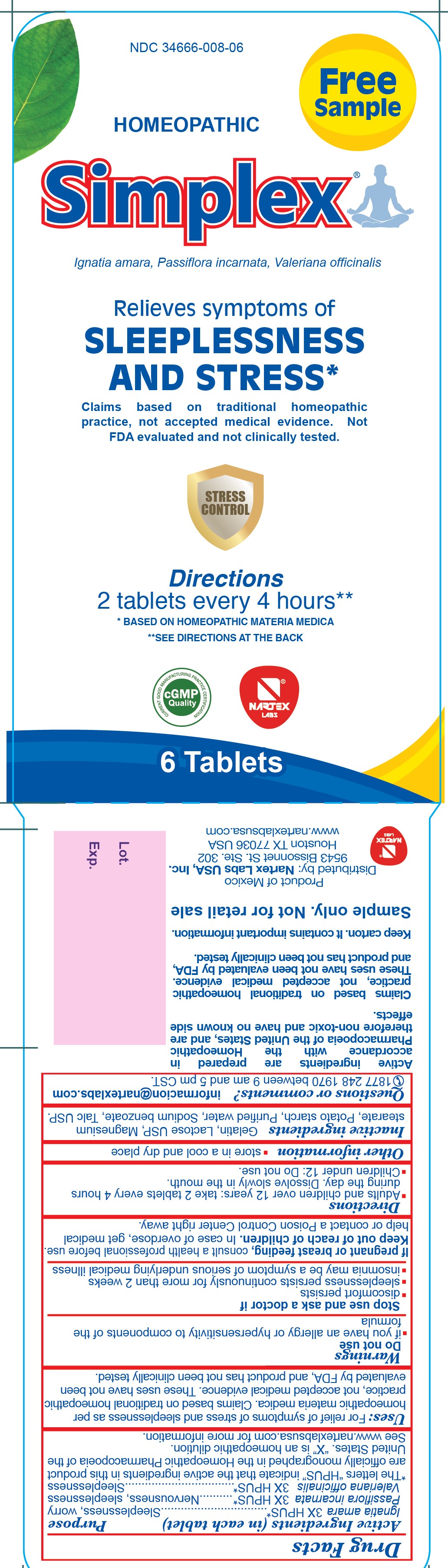 DRUG LABEL: Simplex
NDC: 34666-008 | Form: TABLET
Manufacturer: Nartex Laboratories
Category: homeopathic | Type: HUMAN OTC DRUG LABEL
Date: 20251231

ACTIVE INGREDIENTS: PASSIFLORA INCARNATA FLOWER 3 [hp_X]/1 1; STRYCHNOS IGNATII SEED 3 [hp_X]/1 1; VALERIAN 3 [hp_X]/1 1
INACTIVE INGREDIENTS: WATER; GELATIN; LACTOSE; MAGNESIUM STEARATE; STARCH, POTATO; SODIUM BENZOATE; TALC

ACTIVE INGREDIENT

Ignatia amara 3X HPUS

Passiflora incarnata 3X HPUS

Valeriana officinalis 3X HPUS

PURPOSE

Ignatia Amara 3X HPUS.....................Sleeplessnes, worry

Passiflora incarnata 3X HPUS.............Nervousness, sleeplessness

Valeriana oficinalis 3X HPUS..............Sleeplessness

INDICATIONS AND USAGE

For relief of symptoms of sleeplessness and stress as per homeopathic materia medica. Claims based on traditional homeopathic practice, not accepted medical evidence. These uses have not been evaluated by FDA, and poduct has not been clinically tested.

Do not use

- if you have an allergy or hypersensitivity to components of the formula

Stop use and ask a doctor if

- discomfort persists
- sleeplessness persists continuously for more than 2 weeks. Insomnia may be a symptom of serious underlying medical illness

PREGNANCY OR BREAST FEEDING

If pregnant or breast feeding, consult a health professional before use.

Keep out of reach of children. In case of overdose, get medical help or contact a Poison Control Center right away.

Directions:

- Adults and children over 12 years: take 2 tablets every 4 hours during the day. Dissolve slowly in the mouth.
- Children under 12: Do not use.

STORAGE AND HANDLING

- store in a cool and dry place

INACTIVE INGREDIENT

Gelatin, Lactose USP, Magnesium Stearate, Potato Starch, Purified water, Sodium Benzoate, Talc USP

Questions or Comments?

informacion@nartexlabs.com

1877 248 1970 between 9 am and 5 pm CST

PACKAGE LABEL

NDC 34666-008-06

Homeopathic Simplex

Ignatia amara, Passiflora incaranata, Valeriana officinalis

Relieves symptoms of Sleeplessness and Stress

Claims based on traditional homeopathic practice, not accepted medical evidence. Not FDA evaluated and not clinically tested.

Stress Control

Directions

2 tablets every 4 hours**

* Based on homeopathic materia medica

** See directions at the back

6 tablets